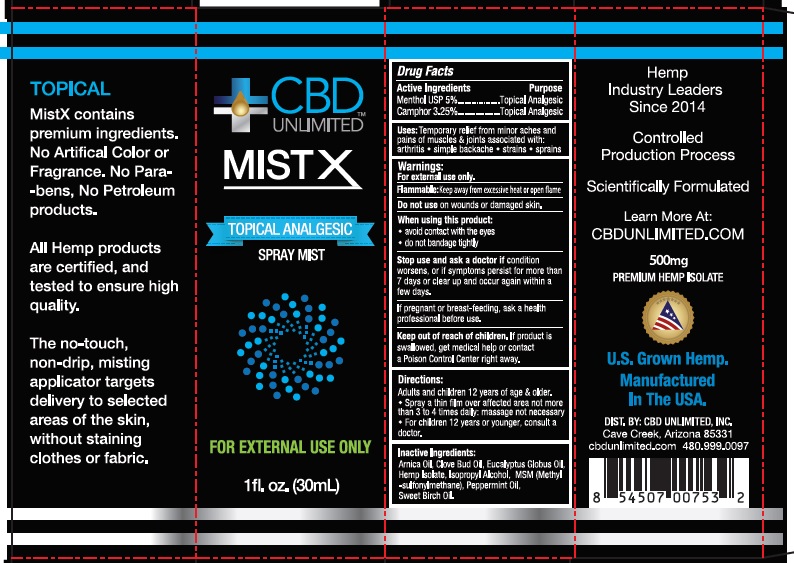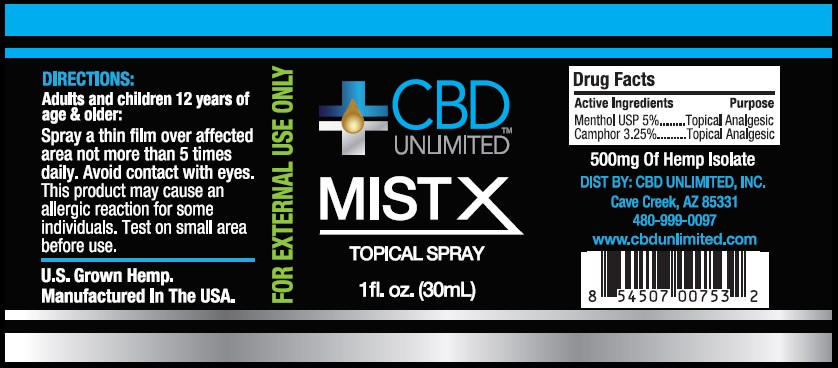 DRUG LABEL: CBD UNLIMITED MISTX TOPICAL ANALGESIC
NDC: 73045-002 | Form: SPRAY
Manufacturer: ENDEXX CORPORATION
Category: otc | Type: HUMAN OTC DRUG LABEL
Date: 20210125

ACTIVE INGREDIENTS: MENTHOL 5 g/100 mL; CAMPHOR OIL 3.25 g/100 mL
INACTIVE INGREDIENTS: HEMP; ARNICA MONTANA FLOWER; CLOVE OIL; EUCALYPTUS OIL; ISOPROPYL ALCOHOL; DIMETHYL SULFONE; PEPPERMINT OIL; METHYL SALICYLATE

CBD UNLIMITED MISTX TOPICAL ANALGESIC

Active ingredient

Menthol USP 5%
Camphor 3.25%

Purpose

Topical Analgesic

Inactive ingredients

Arnica Oil, Clove Bud Oil, Eucalyptus Globus Oil, Hemp, Isopropyl Alcohol, MSM (Methylsulfonylmethane), Peppermint Oil, Sweet Birch Oil.

Uses

Temporary relief from minor aches and pains of muscles & joints associated with: arthritis, simple backache, strains, sprains

Warnings:

For external use only.

Flammable: Keep away from excessive heat or open flame.

Do not use on wounds or damaged skin.

When using this product: Avoid contact with the eyes. Do not bandage tightly.

Stop use and ask a doctor ifcondition worsens, or if symptoms persist for more than 7 days or clear up and occur again within a few days.

If pregnant or breast-feeding ask a health professional before use.

Keep Out of Reach of Children

If product is swallowed get medical help or contact a Poison Control Center right away.

Keep Out of Reach of Children

If product is swallowed get medical help or contact a Poison Control Center right away.

Directions:

Adults and children 12 years of age & older. Spray a thin flim over affected area not more than 3 to 4 times daily: massage not necessary, for children 12 years or younger, consult a doctor.

Distributed By:

CBD UNLIMITED INC

Principal Display Panel

CBD UNLIMITED MISTX

TOPICAL ANALGESIC

1 fl. oz. (30mL) Spray